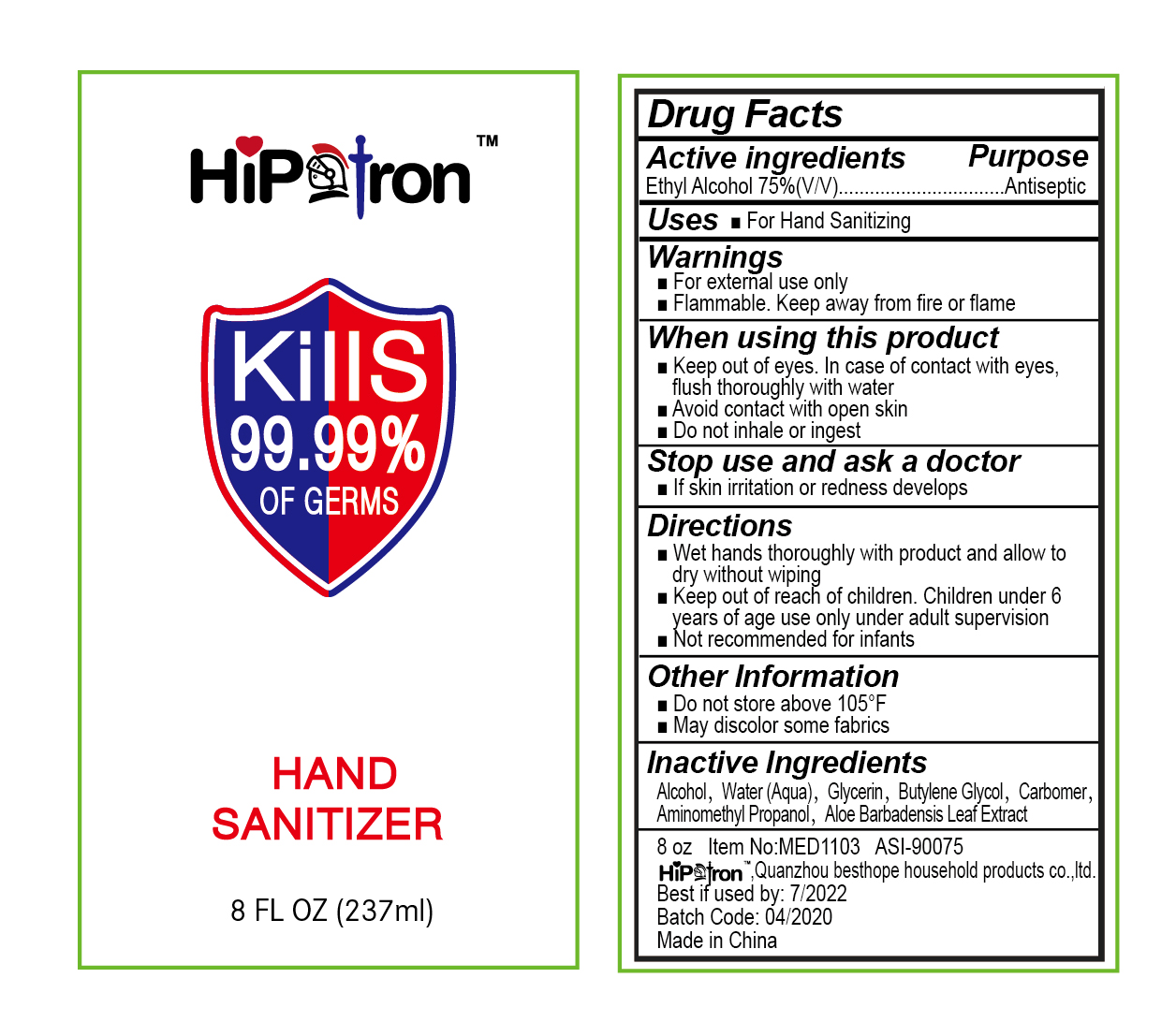 DRUG LABEL: Hand Sanitizer
NDC: 50049-001 | Form: GEL
Manufacturer: QUANZHOU BESTHOPE HOUSEHOLD PRODUCTS CO., LTD.
Category: otc | Type: HUMAN OTC DRUG LABEL
Date: 20200404

ACTIVE INGREDIENTS: ALCOHOL 75 mL/100 mL
INACTIVE INGREDIENTS: WATER; ALOE VERA LEAF; BUTYLENE GLYCOL; CARBOMER 934; GLYCERIN; AMINOMETHYL PROPANEDIOL

50049-001 Hand Sanitizer

Active ingredient

Ethyl Alcohol 75% v/v

Purpose

Antiseptic

Uses

For Hand Sanitizing

Warnings

■Keep out of eyes. In case of contact with eyes,
flush thoroughly with water
■Avoid contact with open skin
■Do not inhale or ingest
Stop use and ask a doctor
■If skin iritation or redness develops

■Keep out of reach of children. Children under 6
years of age use only under adult supervision
■Not recommended for infants

Directions

■Wet hands thoroughly with product and allow to dry without wiping

Other information

1 Do not store above 105°F
1 May discolor some fabrics

Inactive ingredients

Alcohol, Water (Aqua), Glycerin, Butylene Glycol, Carbomer,
Aminomethyl Propanol, Aloe Barbadensis Leaf Extract